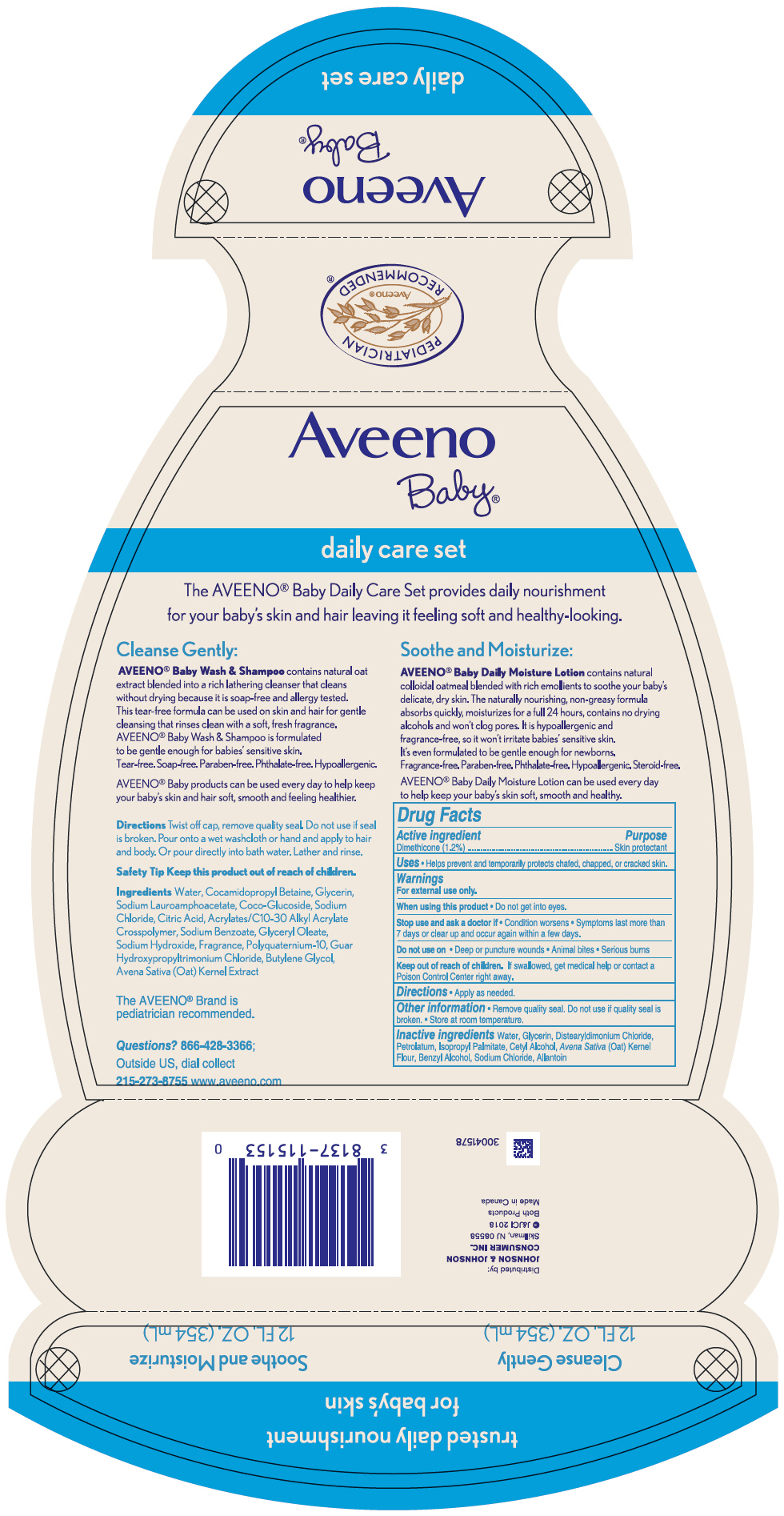 DRUG LABEL: Aveeno Baby Daily Care Set
NDC: 69968-0592 | Form: KIT | Route: TOPICAL
Manufacturer: Kenvue Brands LLC
Category: otc | Type: HUMAN OTC DRUG LABEL
Date: 20241105

ACTIVE INGREDIENTS: DIMETHICONE 12 mg/1 mL
INACTIVE INGREDIENTS: WATER; GLYCERIN; DISTEARYLDIMONIUM CHLORIDE; PETROLATUM; ISOPROPYL PALMITATE; CETYL ALCOHOL; OATMEAL; BENZYL ALCOHOL; SODIUM CHLORIDE; ALLANTOIN

Drug Facts

Active ingredient

Dimethicone 1.2%

Purpose

Skin Protectant

Uses

- Helps prevent and temporarily protects chafed, chapped or cracked skin

Warnings

For external use only

When using this product

- Do not get into eyes

Stop use and ask a doctor if

- Condition worsens
- Symptoms last more than 7 days or clear up and occur again within a few days

Do not use on

- Deep or puncture wounds
- Animal bites
- Serious burns

Keep out of reach of children. If swallowed, get medical help or contact a Poison Control Center right away.

Directions

- Apply as needed.

Other information

- Remove quality seal. Do not use if quality seal is broken.
- Store at room temperature.

Inactive ingredients

Water, Glycerin, Distearyldimonium Chloride, Petrolatum, Isopropyl Palmitate, Cetyl Alcohol, Avena Sativa (Oat) Kernel Flour, Benzyl Alcohol, Sodium Chloride, Allantoin

Questions?

866-428-3366; Outside US, dial collect 215-273-8755 www.aveeno.com

Distributed by:
JOHNSON & JOHNSON
CONSUMER INC.
Skillman, NJ 08558

PRINCIPAL DISPLAY PANEL - Kit Container

Aveeno
Baby®

daily care set

trusted daily nourishment
for baby's skin

Cleanse Gently
12 FL. OZ. (354 mL)

Soothe and Moisturize
12 FL. OZ. (354 mL)